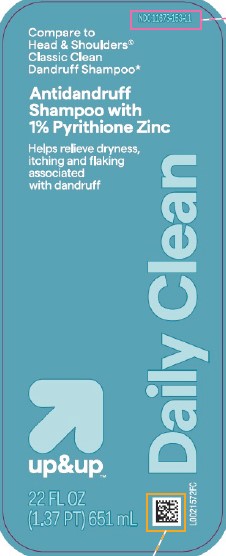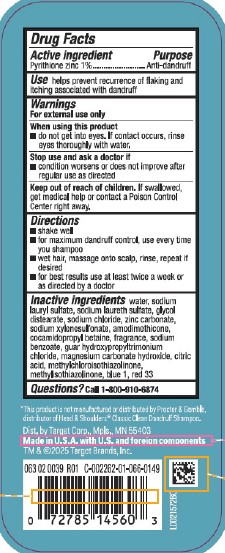 DRUG LABEL: Everyday Clean Dandruff
NDC: 11673-153 | Form: SHAMPOO
Manufacturer: Target Corporation
Category: otc | Type: HUMAN OTC DRUG LABEL
Date: 20260218

ACTIVE INGREDIENTS: PYRITHIONE ZINC 10 mg/1 mL
INACTIVE INGREDIENTS: WATER; SODIUM LAURYL SULFATE; SODIUM LAURETH SULFATE; GLYCOL DISTEARATE; SODIUM CHLORIDE; ZINC CARBONATE; SODIUM XYLENESULFONATE; AMODIMETHICONE (800 CST); COCAMIDOPROPYL BETAINE; SODIUM BENZOATE; GUAR HYDROXYPROPYLTRIMONIUM CHLORIDE (1.7 SUBSTITUENTS PER SACCHARIDE); MAGNESIUM CARBONATE HYDROXIDE; CITRIC ACID MONOHYDRATE; METHYLCHLOROISOTHIAZOLINONE; METHYLISOTHIAZOLINONE; FD&C BLUE NO. 1; D&C RED NO. 33

Up & Up 153.008/153BD
Everyday Clean Dandruff Shampoo

Active ingredient

Pyrithione zinc 1%

Purpose

Anti-dandruff

Use

helps prevent recurrence of flaking and itching associated with dandruff

Warnings

For external use only

When using this product

- do not get into eyes. If contact occurs, rinse eyes thoroughly with water.

Stop use and ask a doctor if

- condition worsens or does not improve after regular use as directed

Keep out of reach of children.

If swallowed, get medical help or contact a Poison Control Center right away.

Directions

- shake well
- for maximum dandruff control, use every time you shampoo
- wet hair, massage onto scalp, rinse, repeat if desired
- for best results use at least twice a week or as directed by a doctor

Inactive ingredients

water, sodium lauryl sulfate, sodium laureth sulfate, glycol distearate, sodium chloride, zinc carbonate, sodium xylenesulfonate, amodimethicone, cocamidopropyl betaine, fragrance, sodium benzoate, guar hydroxypropyltrimonium chloride, magnesium carbonate hydroxide, citric acid, methylchloroisothiazolinone, methylisothiazolinone, blue 1, red 33

Questions?

Call 1-800-910-6874

Disclaimer

*This product is not manufactured or distributed by Procter & Gamble, dstributor of Head & ShouldersClassic Clean Dandruff Shampoo.

Adverse Reactions

Dist. by Target Corp., Mpls., MN 55403

Made in U.S.A. with U.S. and foreign components

TM & © 2025 Target Brands, Inc.

Principal display panel

NDC 11673-153-11

Compare to Head & Shoulders®Classic Clean Dandruff Shampoo*

Antidandruff Shampoo with 1% Pyrithione Zinc

Helps relieve dryness, itching and flaking associated with dandruff

Daily Clean

up & up™

22 FL OZ (1.37 PT) 651 mL